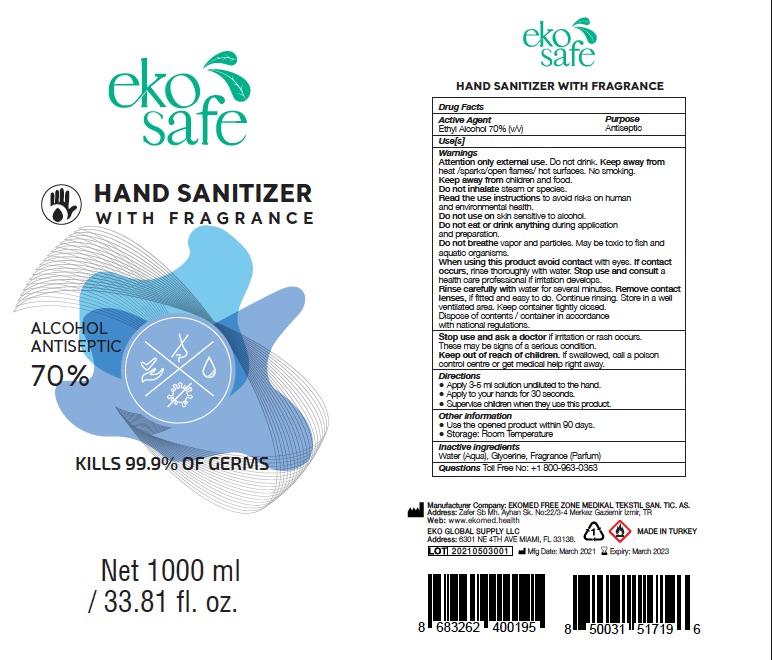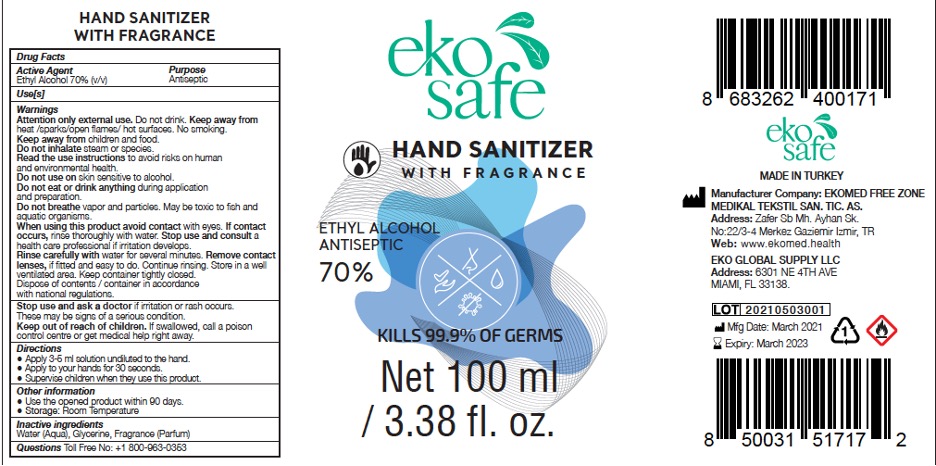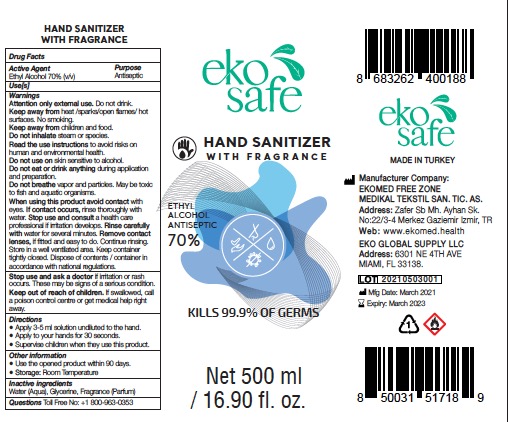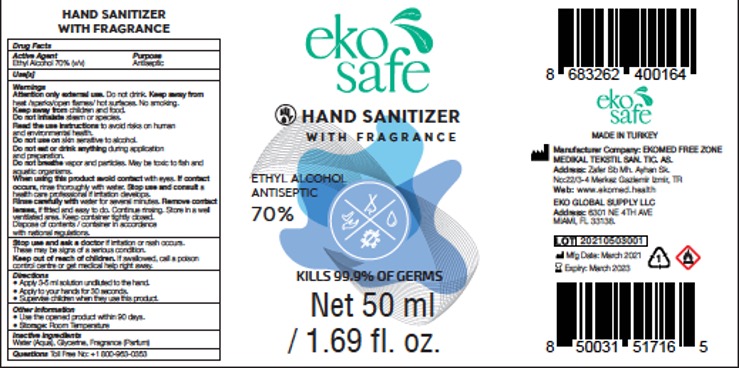 DRUG LABEL: Ekosafe 70%
NDC: 81874-004 | Form: SPRAY
Manufacturer: EKOWIPE HYGIENE AND CLEANING TECHNOLOGIES LLC
Category: otc | Type: HUMAN OTC DRUG LABEL
Date: 20210824

ACTIVE INGREDIENTS: ALCOHOL 35 mL/50 mL
INACTIVE INGREDIENTS: GLYCERIN; CHLORHEXIDINE GLUCONATE; FRAGRANCE LAVENDER & CHIA F-153480; WATER

Ekosafe 70% with Fragrance

Active ingredient

Ethyl alcohol 70%

Purpose

Antiseptic

Uses

- For hand washing to decrease bacteria on the skin
- recommended for repeated use

Warnings

For external use only

Flammable, keep away from fire or flame.

Do not use

in the eyes

Stop use and ask a doctor if

- irritation and redness develop
- condition persists for more than 72 hours

Keep out of reach of children.

If swallowed, get medical help or contact a Poison Control Center right away.

Directions

Wet hands thoroughly with product and allow to dry without wiping

Inactive ingredients

Water, Glycerin, Triethanolamine, Propylene Glycol, Carbomer, Perfum

Questions or comments?

+1 800-963-0353

Package Labeling: Hand Sanitizer with Fragrance

1000 ml NDC 81874-004-01

Package Labeling: Hand Sanitizer with Fragrance 500 ml

100 ml NDC 81874-004-02

Package Labeling: Hand Sanitizer with Fragrance 1000 ml.

1000 ml NDC 81874-004-03

Package Labeling: Hand Sanitizer with Fragrance 50 ml

50 ml NDC 81874-004-04